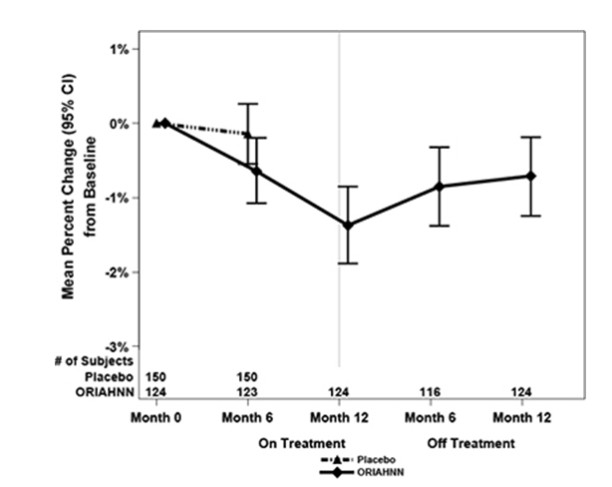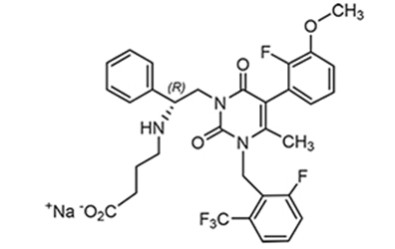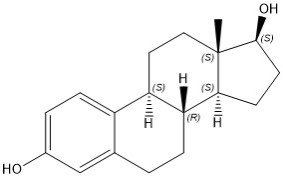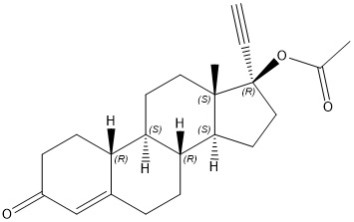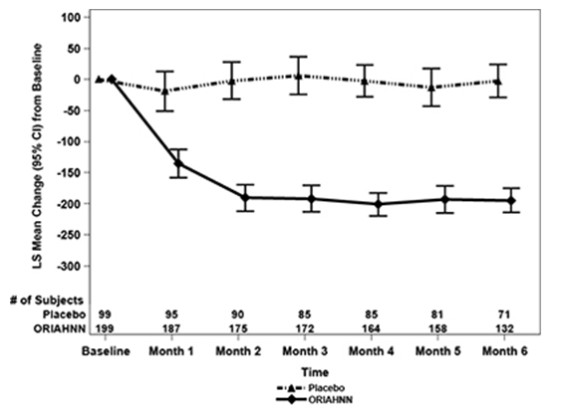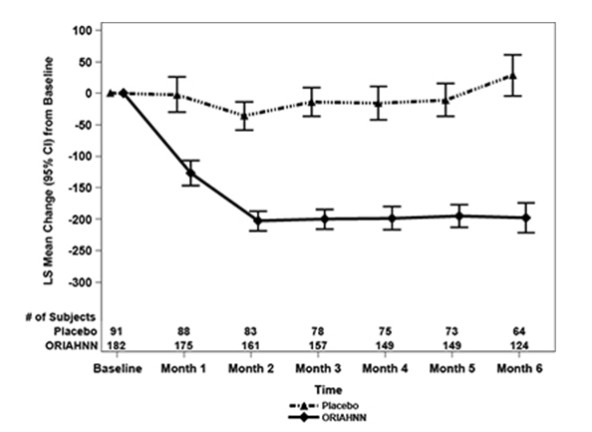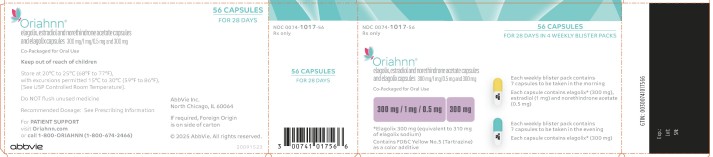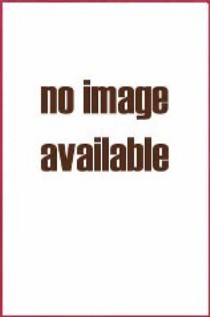 DRUG LABEL: Oriahnn
NDC: 0074-1017 | Form: KIT | Route: ORAL
Manufacturer: AbbVie Inc.
Category: prescription | Type: HUMAN PRESCRIPTION DRUG LABEL
Date: 20251219

ACTIVE INGREDIENTS: ELAGOLIX SODIUM 300 mg/1 1; NORETHINDRONE 0.5 mg/1 1; ESTRADIOL 1 mg/1 1; ELAGOLIX SODIUM 300 mg/1 1
INACTIVE INGREDIENTS: SODIUM CARBONATE; POLYETHYLENE GLYCOL 3350; CROSPOVIDONE, UNSPECIFIED; SILICON DIOXIDE; MAGNESIUM STEARATE; POLYVINYL ALCOHOL, UNSPECIFIED; TITANIUM DIOXIDE; POLYETHYLENE GLYCOL, UNSPECIFIED; TALC; WATER; LACTOSE MONOHYDRATE; STARCH, CORN; COPOVIDONE K25-31; HYPROMELLOSE, UNSPECIFIED; TRIACETIN; FD&C RED NO. 40; FD&C YELLOW NO. 5; FD&C YELLOW NO. 6; GELATIN, UNSPECIFIED; SHELLAC; ALCOHOL; ISOPROPYL ALCOHOL; BUTYL ALCOHOL; PROPYLENE GLYCOL; AMMONIA; FERROSOFERRIC OXIDE; POTASSIUM HYDROXIDE; SODIUM CARBONATE; POLYETHYLENE GLYCOL 3350; CROSPOVIDONE, UNSPECIFIED; SILICON DIOXIDE; MAGNESIUM STEARATE; POLYVINYL ALCOHOL, UNSPECIFIED; TITANIUM DIOXIDE; POLYETHYLENE GLYCOL, UNSPECIFIED; TALC; WATER; FD&C BLUE NO. 2; FERRIC OXIDE YELLOW; GELATIN, UNSPECIFIED; SHELLAC; ALCOHOL; ISOPROPYL ALCOHOL; BUTYL ALCOHOL; PROPYLENE GLYCOL; AMMONIA; FERROSOFERRIC OXIDE; POTASSIUM HYDROXIDE

HIGHLIGHTS OF PRESCRIBING INFORMATION

These highlights do not include all the information needed to use ORIAHNN safely and effectively. See full prescribing information for ORIAHNN.
ORIAHNN® (elagolix, estradiol, and norethindrone acetate capsules; elagolix capsules), co-packaged for oral use
Initial U.S. Approval: 2020

WARNING: THROMBOEMBOLIC DISORDERS AND VASCULAR EVENTS

See full prescribing information for complete boxed warning.

- Estrogen and progestin combinations, including ORIAHNN, increase the risk of thrombotic or thromboembolic disorders, especially in women at increased risk for these events. (5.1)
- ORIAHNN is contraindicated in women with current or a history of thrombotic or thromboembolic disorders and in women at increased risk for these events including women over 35 years of age who smoke or women with uncontrolled hypertension. (4)

1 INDICATIONS AND USAGE

ORIAHNN is a combination of elagolix, a gonadotropin-releasing hormone (GnRH) receptor antagonist, estradiol, an estrogen, and norethindrone acetate, a progestin, indicated for the management of heavy menstrual bleeding associated with uterine leiomyomas (fibroids) in premenopausal women. (1)

Limitation of Use:

- Use of ORIAHNN should be limited to 24 months due to the risk of continued bone loss, which may not be reversible. (1)

2 DOSAGE AND ADMINISTRATION

One capsule (elagolix 300 mg, estradiol 1 mg, norethindrone acetate 0.5 mg) in the morning and one capsule (elagolix 300 mg) in the evening for up to 24 months. (2.1)

3 DOSAGE FORMS AND STRENGTHS

- Morning (AM) capsule: elagolix 300 mg, estradiol 1 mg, norethindrone acetate 0.5 mg. (3)
- Evening (PM) capsule: elagolix 300 mg. (3)

4 CONTRAINDICATIONS

- High risk of arterial, venous thrombotic, or thromboembolic disorder. (4)
- Pregnancy. (4)
- Known osteoporosis. (4)
- Current or history of breast cancer or other hormonally-sensitive malignancies. (4)
- Known liver impairment or disease. (4)
- Undiagnosed abnormal uterine bleeding. (4)
- Known hypersensitivity to ingredients of ORIAHNN. (4)
- Organic anion transporting polypeptide (OATP)1B1 inhibitors that are known or expected to significantly increase elagolix plasma concentrations. (4)

5 WARNINGS AND PRECAUTIONS

- Thromboembolic Disorders and Vascular Events: Discontinue ORIAHNN if an arterial or venous thrombotic, cardiovascular, or cerebrovascular event occurs. Stop ORIAHNN if there is sudden unexplained partial or complete loss of vision, proptosis, diplopia, papilledema, or retinal vascular lesions and evaluate for retinal vein thrombosis immediately. (5.1)
- Bone Loss: Duration-dependent decreases in bone mineral density (BMD) that may not be completely reversible. Baseline and periodic BMD assessments are recommended. Assess risk-benefit for women with additional risk factors for bone loss. (5.2)
- Suicidal Ideation and Mood Disorders: Advise patients to seek medical attention for suicidal ideation, suicidal behavior, new onset or worsening depression, anxiety, or other mood changes. (5.4)
- Hepatic Impairment and Transaminase Elevations: Counsel patients on signs and symptoms of liver injury. (5.5)
- Elevated Blood Pressure: Do not use in women with uncontrolled hypertension. For women with well-controlled hypertension, continue to monitor blood pressure and stop ORIAHNN if blood pressure rises significantly. (5.6)
- Change in Menstrual Bleeding Pattern and Reduced Ability to Recognize Pregnancy: Advise women to use non-hormonal contraception during treatment and for 28 days after discontinuing ORIAHNN. ORIAHNN may delay the ability to recognize the occurrence of a pregnancy because it alters menstrual bleeding. Perform pregnancy testing if pregnancy is suspected and discontinue ORIAHNN if pregnancy is confirmed. (5.8)
- Risk of Allergic Reactions Due to the Inactive Ingredient (FD&C Yellow No 5): This product contains FD&C Yellow No. 5 (tartrazine), which may cause allergic-type reactions (including bronchial asthma) in certain susceptible persons. (5.12)

6 ADVERSE REACTIONS

Most common adverse reaction (>5%) in clinical trials were hot flushes, headache, fatigue, metrorrhagia. (6.1)

To report SUSPECTED ADVERSE REACTIONS, contact AbbVie Inc. at 1–800–633–9110 or FDA at 1-800-FDA-1088 or www.fda.gov/medwatch

7 DRUG INTERACTIONS

See full prescribing information for a list of clinically important drug interactions. (7)

FULL PRESCRIBING INFORMATION

WARNING: THROMBOEMBOLIC DISORDERS AND VASCULAR EVENTS

- Estrogen and progestin combinations, including ORIAHNN, increase the risk of thrombotic or thromboembolic disorders including pulmonary embolism, deep vein thrombosis, stroke and myocardial infarction, especially in women at increased risk for these events [see Warnings and Precautions (5.1)].
- ORIAHNN is contraindicated in women with current or a history of thrombotic or thromboembolic disorders and in women at increased risk for these events, including women over 35 years of age who smoke and women with uncontrolled hypertension [see Contraindications (4)].

1 INDICATIONS AND USAGE

ORIAHNN is indicated for the management of heavy menstrual bleeding associated with uterine leiomyomas (fibroids) in premenopausal women.

Limitation of Use:

Use of ORIAHNN should be limited to 24 months due to the risk of continued bone loss, which may not be reversible [see Dosage and Administration (2.1) and Warnings and Precautions (5.2)].

2 DOSAGE AND ADMINISTRATION

2.1 Important Dosing Information

- Exclude pregnancy before starting ORIAHNN or start ORIAHNN within 7 days from the onset of menses [see Use in Specific Populations (8.1) and (8.3)].
- The recommended dosage of ORIAHNN is:
  ○ One elagolix 300 mg, estradiol 1 mg, and norethindrone acetate 0.5 mg capsule in the morning (AM), and
  ○ One elagolix 300 mg capsule in the evening (PM).
- Take the morning and evening capsules at approximately the same time each day, with or without food.
- The recommended duration of treatment with ORIAHNN is 24 months [see Warnings and Precautions (5.2)].

2.2 Missed Dose

Instruct the patient to take the missed dose of ORIAHNN within 4 hours of the time that it was supposed to be taken and then the next dose at the usual time. If more than 4 hours have passed since a capsule is usually taken, instruct the patient not to take the missed dose and take the next dose at the usual time. Take only one morning capsule and one evening capsule per day.

3 DOSAGE FORMS AND STRENGTHS

ORIAHNN consists of two capsules:

- The morning (AM) capsule is white and yellow, printed with “EL300 AM” containing 300 mg elagolix, 1 mg estradiol, and 0.5 mg norethindrone acetate.
- The evening (PM) capsule is white and light blue, printed with “EL300 PM” containing 300 mg elagolix.

4 CONTRAINDICATIONS

ORIAHNN is contraindicated in women:

- With a high risk of arterial, venous thrombotic, or thromboembolic disorders [see Boxed Warning and Warnings and Precautions (5.1)]. Examples include women over 35 years of age who smoke, and women who are known to have:
  ○ current or history of deep vein thrombosis or pulmonary embolism
  ○ vascular disease (e.g., cerebrovascular disease, coronary artery disease, peripheral vascular disease)
  ○ thrombogenic valvular or thrombogenic rhythm diseases of the heart (for example, subacute bacterial endocarditis with valvular disease, or atrial fibrillation)
  ○ inherited or acquired hypercoagulopathies
  ○ uncontrolled hypertension
  ○ headaches with focal neurological symptoms or have migraine headaches with aura if over age 35
- Who are pregnant. Exposure to ORIAHNN early in pregnancy may increase the risk of early pregnancy loss [see Use in Specific Populations (8.1)].
- With known osteoporosis because of the risk of further bone loss [see Warnings and Precautions (5.2)].
- With current or history of breast cancer or other hormonally-sensitive malignancies, and with increased risk for hormonally-sensitive malignancies [see Warnings and Precautions (5.3)].
- With known hepatic impairment or disease [see Warnings and Precautions (5.5)].
- With undiagnosed abnormal uterine bleeding.
- With known anaphylactic reaction, angioedema, or hypersensitivity to ORIAHNN or any of its components.
- Taking inhibitors of organic anion transporting polypeptide (OATP)1B1 (a hepatic uptake transporter) that are known or expected to significantly increase elagolix plasma concentrations [see Drug Interactions (7.2)].

5 WARNINGS AND PRECAUTIONS

5.1 Thromboembolic Disorders and Vascular Events

ORIAHNN is contraindicated in women with current or history of thrombotic or thromboembolic disorders and in women at increased risk for these events [see Contraindications (4)]. In the Phase 3 clinical trials (Studies UF-1, UF-2, and UF-3), two thrombotic events occurred in 453 ORIAHNN-treated women (thrombosis in the calf and pulmonary embolism) [see Adverse Reactions (6.1) and Clinical Studies (14)]. Estrogen and progestin combinations, including the estradiol/norethindrone acetate component of ORIAHNN, increase the risk of thrombotic or thromboembolic disorders, including pulmonary embolism, deep vein thrombosis, stroke, and myocardial infarction, especially in women at high risk for these events. In general, the risk is greatest among women over 35 years of age who smoke, and women with uncontrolled hypertension, dyslipidemia, vascular disease, or obesity.

Discontinue ORIAHNN if an arterial or venous thrombotic, cardiovascular, or cerebrovascular event occurs or is suspected. If feasible, discontinue ORIAHNN at least 4 to 6 weeks before surgery of the type associated with an increased risk of thromboembolism, or during periods of prolonged immobilization.

Stop ORIAHNN immediately if there is sudden unexplained partial or complete loss of vision, proptosis, diplopia, papilledema, or retinal vascular lesions and evaluate for retinal vein thrombosis as these have been reported in patients receiving estrogens and progestins.

5.2 Bone Loss

ORIAHNN is contraindicated in women with known osteoporosis [see Contraindications (4)]. ORIAHNN may cause a decrease in bone mineral density (BMD) in some patients. BMD loss is greater with increasing duration of use and may not be completely reversible after stopping treatment [see Adverse Reactions (6.1)].

In the Phase 3 clinical trials (Studies UF-1, UF-2, and UF-3) [see Clinical Studies (14)], seven out of 453 (1.5%) ORIAHNN-treated women experienced fractures, including one (0.2%) with a fragility fracture, compared to one out of 196 (0.5%) placebo-treated women (patient had a non-fragility fracture). Five of the seven ORIAHNN-treated women reported these fractures in the post-treatment follow-up period. The impact of BMD decreases on long-term bone health and future fracture risk in premenopausal women is unknown.

Consider the benefits and risks of ORIAHNN treatment in patients with a history of a low-trauma fracture or other risk factors for osteoporosis or bone loss, including taking medications that may decrease BMD (e.g., systemic or chronic inhaled corticosteroids, anticonvulsants, or proton pump inhibitors).

Assessment of BMD by dual-energy X-ray absorptiometry (DXA) is recommended at baseline and periodically thereafter. Consider discontinuing ORIAHNN if the risk associated with bone loss exceeds the potential benefit of treatment. Limit the duration of use to 24 months to reduce the extent of bone loss [see Indications and Usage (1) and Dosage and Administration (2.1)].

Although the effect of supplementation with calcium and vitamin D was not studied, such supplementation for patients with inadequate dietary intake may be beneficial.

5.3 Hormonally-Sensitive Malignancies

ORIAHNN is contraindicated in women with current or history of breast cancer and in women at increased risk for hormonally-sensitive malignancies, such as those with mutations in BRCA genes [see Contraindications (4)].

In the Phase 3 clinical trials (Studies UF-1, UF-2, and UF-3), two (0.4%) cases of breast cancer in 453 ORIAHNN-treated women were observed. No breast cancer cases were seen in placebo-treated women [see Adverse Reactions (6.1)].

The use of estrogen alone and estrogen plus progestin has been reported to result in an increase in abnormal mammograms requiring further evaluation. Surveillance measures, such as breast examinations and regular mammography, are recommended. Discontinue ORIAHNN if a hormonally-sensitive malignancy is diagnosed.

5.4 Suicidal Ideation, Suicidal Behavior, and Exacerbation of Mood Disorders

In Phase 3 placebo-controlled clinical trials (Studies UF-1 and UF-2), ORIAHNN-treated women had a higher incidence (3%) of depression, depressed mood, and/or tearfulness compared to placebo-treated women (1%) [see Adverse Reactions (6.1)]. Suicidal ideation and behavior, including a completed suicide, occurred in women treated with lower doses of elagolix in clinical trials conducted for a different indication.

Promptly evaluate patients with depressive symptoms to determine whether the risks of continued therapy outweigh the benefits. Patients with new or worsening depression, anxiety, or other mood changes should be referred to a mental health professional, as appropriate. Advise patients to seek immediate medical attention for suicidal ideation and behavior.

Reevaluate the benefits and risks of continuing ORIAHNN if such events occur.

5.5 Hepatic Impairment and Transaminase Elevations

Contraindication in Patients with Hepatic Impairment

ORIAHNN is contraindicated in women with known hepatic impairment or disease [see Contraindications (4), Use in Specific Populations (8.7), and Clinical Pharmacology (12.3)].

Transaminase Elevations

In Phase 3 placebo-controlled clinical trials (Studies UF-1 and UF-2), elevations (> 3 times the upper limit of the reference range) in alanine aminotransferase (ALT) and aspartate aminotransferase (AST) occurred in 1.1% (4/379) and 1.3% (5/379) of ORIAHNN-treated patients, respectively, compared to no elevations in placebo. Transaminases peaked at 8 times the upper limit for ALT and 6 times the upper limit for AST. No pattern in time to onset of these liver transaminase elevations was identified. Transaminase levels returned to baseline within 4 months after peak values in these patients.

Instruct patients to promptly seek medical attention in case of symptoms or signs that may reflect liver injury, such as jaundice [see Adverse Reactions (6.1)].

5.6 Elevated Blood Pressure

ORIAHNN is contraindicated in women with uncontrolled hypertension [see Contraindications (4)]. In Studies UF-1 and UF-2, a maximum mean increase in systolic blood pressure of 5.1 mmHg [95% confidence interval (CI) 2.68, 7.59] occurred at Month 5, and a maximum mean increase in diastolic blood pressure of 2.1 mmHg (95% CI 0.43, 3.84) occurred at Month 4 in ORIAHNN-treated women, as compared to placebo-treated women [see Adverse Reactions (6.1)].

For women with well-controlled hypertension, continue to monitor blood pressure and stop ORIAHNN if blood pressure rises significantly. Monitor blood pressure in normotensive women treated with ORIAHNN.

5.7 Gallbladder Disease or History of Cholestatic Jaundice

Studies among estrogen users suggest a small increased relative risk of developing gallbladder disease. For women with a history of cholestatic jaundice associated with past estrogen use or with pregnancy, assess the risk-benefit of continuing therapy. Discontinue ORIAHNN if jaundice occurs.

5.8 Change in Menstrual Bleeding Pattern and Reduced Ability to Recognize Pregnancy

ORIAHNN may delay the ability to recognize the occurrence of a pregnancy because it may reduce the intensity, duration, and amount of menstrual bleeding [see Adverse Reactions (6.1)]. Perform pregnancy testing if pregnancy is suspected, and discontinue ORIAHNN if pregnancy is confirmed [see Use in Specific Populations (8.1, 8.3)].

The effect of hormonal contraceptives on the efficacy of ORIAHNN is unknown. Advise women to use non-hormonal contraception during treatment and for 28 days after discontinuing ORIAHNN [see Use in Specific Populations (8.1, 8.3)].

5.9 Effects on Carbohydrate and Lipid Metabolism

ORIAHNN may decrease glucose tolerance and result in increased glucose levels. More frequent monitoring in ORIAHNN-treated women with prediabetes and diabetes may be needed.

In women with pre-existing hypertriglyceridemia, estrogen therapy may be associated with elevations of plasma triglycerides leading to pancreatitis. Use of elagolix is associated with increases in total cholesterol, low-density lipoprotein cholesterol (LDL-C), high-density lipoprotein cholesterol (HDL-C), and serum triglycerides. Monitor lipid levels and consider discontinuing ORIAHNN if hypercholesterolemia or hypertriglyceridemia worsens [see Adverse Reactions (6.1)].

5.10 Alopecia

In Phase 3 clinical trials (Studies UF-1 and UF-2), more women experienced alopecia, hair loss, and hair thinning with ORIAHNN (3.5%) compared to placebo (1.0%). In almost one-third (4/14) of affected ORIAHNN-treated women, alopecia was a reason for discontinuing treatment. No specific pattern was described. In the majority of affected women, hair loss was continuing when ORIAHNN was stopped. Whether the hair loss is reversible is unknown. Consider discontinuing ORIAHNN if hair loss becomes a concern [see Adverse Reactions (6.1)].

5.11 Effect on Other Laboratory Results

The use of estrogen and progestin combinations may raise serum concentrations of binding proteins (e.g., thyroid-binding globulin, corticosteroid-binding globulin), which may reduce the free thyroid or corticosteroid hormone levels. Patients with hypothyroidism and hypoadrenalism may require higher doses of thyroid hormone or cortisol replacement therapy, respectively.

The use of estrogen and progestin may also affect the levels of sex hormone-binding globulin, coagulation factors, lipids, and glucose [see Pharmacodynamics (12.2)].

5.12 Risk of Allergic Reactions Due to the Inactive Ingredient (FD&C Yellow No. 5)

ORIAHNN contains FD&C Yellow No. 5 (tartrazine), which may cause allergic-type reactions (including bronchial asthma) in certain susceptible persons. Although the overall incidence of FD&C Yellow No. 5 (tartrazine) sensitivity in the general population is low, it is frequently seen in patients who also have aspirin hypersensitivity.

6 ADVERSE REACTIONS

The following serious adverse reactions are discussed elsewhere in labeling:

- Thromboembolic Disorders and Vascular Events [see Warnings and Precautions (5.1)]
- Bone Loss [see Warnings and Precautions (5.2)]
- Suicidal Ideation, Suicidal Behavior, and Exacerbation of Mood Disorders [see Warnings and Precautions (5.4)]
- Hepatic Transaminase Elevations [see Warnings and Precautions (5.5)]
- Elevated Blood Pressure [see Warnings and Precautions (5.6)]
- Effects on Carbohydrate and Lipid Metabolism [see Warnings and Precautions (5.9)]
- Alopecia [see Warnings and Precautions (5.10)]

6.1 Clinical Trials Experience

Because clinical trials are conducted under widely varying conditions, adverse reaction rates observed in the clinical trials of a drug cannot be directly compared to rates in the clinical trials of another drug and may not reflect the rates observed in clinical practice.

The safety of ORIAHNN was evaluated in two 6-month, randomized, double-blind, placebo-controlled trials (Studies UF-1 and UF-2), in which 790 premenopausal women received at least 1 dose of ORIAHNN (n=395), elagolix 300 mg twice daily (n=199), or placebo (n=196) [see Clinical Studies (14)]. Women who completed 6-month treatment in either Study UF-1 or Study UF-2 and met eligibility criteria (n=433) entered a 6-month extension study (Study UF-3), receiving either ORIAHNN (n=276) or elagolix 300 mg twice daily (n=157). Elagolix 300 mg twice daily is not an approved dosage but was included as a reference arm. A total of 341 women received ORIAHNN for 6 months and 182 women received ORIAHNN for 12 months.

Serious Adverse Events

Serious adverse events were reported in three (0.8%) ORIAHNN-treated women in Studies UF-1 and UF-2. Two women had heavy menstrual bleeding and required blood transfusion due to anemia (0.5%) and one woman with history of bariatric surgery had a laparoscopic cholecystectomy due to cholelithiasis.

In Study UF-3, two women were diagnosed with breast cancer. One woman had completed 6 months of treatment with ORIAHNN in Study UF-1 and received 34 additional days of ORIAHNN in Study UF-3 when diagnosed. The second woman had received placebo in Study UF-2 and completed 6 months of ORIAHNN in Study UF-3 when diagnosed [see Warnings and Precautions (5.3)].

Adverse Reactions Leading to Study Discontinuation

In Studies UF-1 and UF-2, the discontinuation rate due to adverse reactions was 10% among ORIAHNN-treated women and 7% among placebo-treated women. The most common adverse reactions leading to study drug discontinuation in the ORIAHNN group were nausea (1%), headache (1%), alopecia (1%), metrorrhagia (1%), menorrhagia (1%), and hot flush (1%). One event each of the following adverse reactions led to study drug discontinuation: affect lability, angina pectoris, depression, hepatic enzyme increased, homicidal ideation, hypertension, irritability, thrombosis.

In women who received ORIAHNN in Studies UF-1 or UF-2 and then in Study UF-3, 4% discontinued treatment due to adverse reactions. Three women discontinued due to serious adverse events (one each for breast cancer, menorrhagia with pelvic pain, and hysterectomy).

Common Adverse Reactions

Adverse reactions reported in ≥5% of ORIAHNN-treated women in Studies UF-1 and UF-2 and at a greater frequency than placebo-treated women are presented in Table 1.

Table 1. Adverse Reactions that Occurred in at Least 5% of Women with Uterine Fibroids Who Received ORIAHNN in Studies UF-1 and UF-2 and at a Greater Incidence Than Placebo
Adverse Reaction | ORIAHNN N=395 | Placebo N=196
Hot flush | 22% | 9%
Headache | 9% | 7%
Fatigue | 6% | 4%
Metrorrhagia | 5% | 1%

The most commonly reported adverse reactions in the blinded extension trial (Study UF-3) were consistent with those in the placebo-controlled trials.

Less Common Adverse Reactions

In Studies UF-1 and UF-2, adverse reactions reported in ≥3% and <5% in the ORIAHNN group and greater incidence than the placebo group included: libido decreased, arthralgia, hypertension, alopecia, mood swings, influenza, abdominal distension, upper respiratory tract infection, menorrhagia, vomiting, and weight increased.

Thromboembolic and Vascular Events

In the Studies UF-1, UF-2, and UF-3, two (0.4%) thrombotic events occurred in 453 ORIAHNN-treated patients (thrombosis in the calf and pulmonary embolism) [see Warnings and Precautions (5.1)]. One obese woman developed thrombosis in the left calf after 30 days of treatment with ORIAHNN. Another woman developed a pulmonary embolism after taking ORIAHNN for approximately 8 months.

Bone Loss

The effect of ORIAHNN on BMD was assessed by dual-energy X-ray absorptiometry (DXA).

In Studies UF-1 and UF-2, there was a greater decrease in BMD in women treated with ORIAHNN for 6 months compared to women treated with placebo. In Study UF-3, continued bone loss was observed in some women who received ORIAHNN for 12 consecutive months. The mean percent change from baseline in lumbar spine BMD at Month 6 (Studies UF-1 and UF-2) and Month 12 (Study UF-3) is presented in Table 2.

Table 2. Mean Percent Change (On-Treatment) from Baseline in Lumbar Spine BMD in Women with Fibroids at Month 6 in Studies UF-1 and UF-2 and Month 12 in Study UF-3
 | Studies UF-1 and UF-2 Treatment Month 6 |  | Study UF-3 Treatment Month 12
 | Placebo | ORIAHNN | ORIAHNN
Number of Subjects | 150 | 305 | 175
Percent Change from Baseline | -0.1 | -0.7 | -1.5
Treatment Difference, % (95% CI) |  | -0.6 (-1.0, -0.1)
CI: Confidence interval

Following 12 months of ORIAHNN treatment in Study UF-3, a decline in lumbar spine BMD of >3% was seen in 27% (48/175) of women and a decline of ≥8% was seen in 1.7% (3/175) of women.

To assess for recovery, the change in BMD over time was analyzed for women who received continuous ORIAHNN treatment for up to 12 months and were then followed after cessation of therapy for an additional 12 months in Study UF-3 (Figure 1). The LS mean percent change from baseline in BMD 12 months after cessation of therapy was -0.72 (95% CI -1.2, -0.2), -0.59 (-1.0, -0.2), and -0.95 (-1.6, -0.3) at the lumbar spine, total hip, and femoral neck, respectively. Twelve months after cessation of ORIAHNN, continued bone loss was observed at the lumbar spine, total hip, and femoral neck in 24%, 32%, and 40% of women, respectively. Partial recovery was observed in 46%, 33%, and 38% and full recovery was observed in 30%, 35%, and 22% of women at these same sites. The time to maximum recovery in women who partially recovered is unknown.

Figure 1. Mean Percent Change From Baseline in Lumbar Spine BMD in Women Who Received 12 Months of ORIAHNN (On-Treatment) and 12 Months of Follow Up (Off Treatment)

Suicidal Ideation, Suicidal Behavior, and Exacerbation of Mood Disorders

In the placebo-controlled trials (Studies UF-1 and UF-2), ORIAHNN was associated with adverse mood changes. Depression, depressed mood, and/or tearfulness were reported in 3% of ORIAHNN-treated women compared to 1% of placebo-treated women. One woman treated with lower dose elagolix alone for another disease completed suicide 2 days after elagolix discontinuation.

Hepatic Transaminase Elevations

In Studies UF-1 and UF-2, elevations of serum ALT and AST with no concurrent elevations of bilirubin were reported.

- ALT elevations to at least 3 times the upper limit of normal (ULN) occurred in 1.1% (4/379) of ORIAHNN-treated women and no placebo-treated women. Peak elevation of ALT almost 8 times the ULN was reported in 1 ORIAHNN-treated woman.
- AST elevations to at least 3 times the ULN occurred in 5/379 (1.3%) in ORIAHNN-treated women and no placebo-treated women. Peak elevation of AST 6 times the ULN was reported in 1 ORIAHNN-treated woman.

Blood Pressure Elevations

There were more ORIAHNN-treated women with systolic blood pressure ≥ 160 mmHg (7.1%) and diastolic blood pressure ≥ 100 mmHg (11.3%) compared to placebo-treated women (3.7% and 6.3%, respectively). The incidence of hypertensive adverse reactions was 3.8% in ORIAHNN-treated women and 3.1% placebo-treated women. One ORIAHNN-treated woman in Study UF-1, with no prior history but with elevated cholesterol levels, had severe hypertension (BP 204/112) and chest pain. ECG was negative. Her hypertension was controlled with anti-hypertensives and she completed Study UF-3.

Changes in Lipid Parameters

Increases in total cholesterol, low-density lipoprotein cholesterol (LDL-C), serum triglycerides, and apolipoprotein B were noted during ORIAHNN treatment in Studies UF-1 and UF-2.

Of the women with Grade 0 LDL-C (<130 mg/dL) at baseline, 1/313 (0.3%) ORIAHNN-treated woman shifted to Grade 3 (≥ 190 mg/dL) compared to no placebo-treated woman. Of those with Grade 1 LDL-C (130 to <160 mg/dL) at baseline, 9/54 (16.7%) ORIAHNN-treated women shifted to Grade 3 compared to no placebo-treated woman. Of those with Grade 2 LDL-C (160 to <190 mg/dL) at baseline, 7/10 (70%) ORIAHNN-treated women shifted to Grade 3 compared to 1/5 (20%) placebo-treated woman.

Alopecia

In Phase 3 placebo-controlled clinical trials (Studies UF-1 and UF-2), 3.5% (14/395) of ORIAHNN-treated women experienced alopecia, hair loss, or hair thinning compared to 1.0% (2/196) of placebo-treated women. No specific pattern in hair loss was observed. In almost one-third (4/14) of affected ORIAHNN-treated women, alopecia was a reason for study drug discontinuation; no placebo-treated women discontinued because of alopecia. In ORIAHNN-treated women, 79% of the cases were mild and 21% were moderate in severity. Hair loss was ongoing at the end of the study for 4 out of 14 women (29%). Of these 4 women, one discontinued treatment due to hair loss, two had ongoing hair loss 12 months after discontinuing ORIAHNN, and one was lost to follow-up. In the remaining 10 women (71%), hair loss either resolved while on treatment or resolved within 24 days to approximately 9 months after discontinuing ORIAHNN.

Resumption of Menses after Discontinuation

After six months of ORIAHNN treatment, resumption of menses was reported by 39%, 68%, and 73% of women within 1, 2, and 6 months, respectively, in Study UF-1 and 39%, 85%, and 92% within 1, 2, and 6 months, respectively, in Study UF-2.

After 12 months of therapy with ORIAHNN (Study UF-1 or Study UF-2 then Study UF-3), resumption of menses was reported by 43%, 82%, and 90% of women within 1, 2, and 6 months after stopping treatment, respectively.

Whether those who did not resume having menses transitioned to a peri-postmenopausal status is unknown.

7 DRUG INTERACTIONS

7.1 Potential for ORIAHNN to Affect Other Drugs

Elagolix (a component of ORIAHNN) is:

- A weak to moderate inducer of cytochrome P450 (CYP3A). Co-administration with ORIAHNN may decrease plasma concentrations of drugs that are substrates of CYP3A.
- A weak inhibitor of CYP2C19. Co-administration with ORIAHNN may increase plasma concentrations of drugs that are substrates of CYP2C19 (see Table 3).
- An inhibitor of efflux transporter P-glycoprotein (P-gp). Co-administration with ORIAHNN may increase plasma concentrations of drugs that are substrates of P-gp (see Table 3).

The effects of co-administration of ORIAHNN on concentrations of concomitant drugs and the clinical recommendations for these drug interactions are summarized in Table 3.

Table 3. Drug Interactions: Effects of ORIAHNN on Other Drugs
Concomitant Drug Class: Drug Name | Effect on Plasma Exposure of Concomitant Drug | Clinical Recommendations
Cardiac glycosides: digoxin | ↑ digoxin | Increase monitoring of digoxin concentrations and potential signs and symptoms of clinical toxicity when initiating ORIAHNN in patients who are taking digoxin. If ORIAHNN is discontinued, increase monitoring of digoxin concentrations.
Benzodiazepines: oral midazolam | ↓ midazolam | Consider increasing the dose of midazolam by no more than 2-fold and individualize midazolam therapy based on the patient’s response.
Statins: rosuvastatin | ↓ rosuvastatin | Monitor lipid levels and adjust the dose of rosuvastatin, if necessary.
Proton pump inhibitors: omeprazole | ↑ omeprazole | No dose adjustment needed for omeprazole 40 mg once daily when co-administered with ORIAHNN. When ORIAHNN is used concomitantly with higher doses of omeprazole, consider dosage reduction of omeprazole.
See Tables 6 and 7 [see Clinical Pharmacology (12.3)].
The direction of the arrow indicates the direction of the change in the area under the curve (AUC) (↑= increase, ↓ = decrease).

7.2 Potential for Other Drugs to Affect ORIAHNN

Elagolix (a component of ORIAHNN) is a substrate of CYP3A, P-gp, and OATP1B1; estradiol and norethindrone acetate are metabolized partially by CYP3A [see Clinical Pharmacology (12.3)]. Concomitant use of ORIAHNN with:

- Strong CYP3A inducers may decrease elagolix, estradiol, and norethindrone plasma concentrations and may result in a decrease of the therapeutic effects of ORIAHNN.
- Rifampin is not recommended. The concomitant use of rifampin increased plasma concentrations of elagolix [see Clinical Pharmacology (12.3)].
- Strong CYP3A inhibitors are not recommended. Concomitant use of ORIAHNN with strong CYP3A inhibitors may increase elagolix, estradiol, and norethindrone plasma concentrations and increase the risk of adverse reactions.
- OATP1B1 inhibitors that are known or expected to significantly increase elagolix plasma concentrations is contraindicated due to increased risk of elagolix-associated adverse reactions [see Contraindications (4)].

8 USE IN SPECIFIC POPULATIONS

8.1 Pregnancy

Risk Summary

Use of ORIAHNN is contraindicated in pregnant women. Exposure to elagolix early in pregnancy may increase the risk of early pregnancy loss. Discontinue ORIAHNN if pregnancy occurs during treatment.

The limited human data with the use of elagolix in pregnant women are insufficient to determine whether there is a risk for major birth defects or miscarriage [see Data].

When pregnant rats and rabbits were orally dosed with elagolix during the period of organogenesis, postimplantation loss was observed in pregnant rats at doses 12 times the maximum recommended human dose (MRHD). Spontaneous abortion and total litter loss were observed in rabbits at doses 4 and 7 times the MRHD. There were no structural abnormalities in the fetuses at exposures up to 25 and 7 times the MRHD for the rat and rabbit, respectively [see Data].

Data

Human Data

There was one pregnancy reported in the 453 women who received ORIAHNN in the Phase 3 uterine fibroids clinical trials. The pregnancy resulted in a spontaneous abortion and the estimated fetal exposure to ORIAHNN occurred during the first 18 days of pregnancy.

Animal Data

Embryofetal development studies were conducted in the rat and rabbit. Elagolix was administered by oral gavage to pregnant rats (25 animals/dose) at doses of 0, 300, 600, and 1200 mg/kg/day and to rabbits (20 animals/dose) at doses of 0, 100, 150, and 200 mg/kg/day during the period of organogenesis (gestation day 6-17 in the rat and gestation day 7-20 in the rabbit).

In rats, maternal toxicity was present at all doses and included six deaths and decreases in body weight gain and food consumption. Increased postimplantation losses were present in the mid dose group, which was 12 times the MRHD based on AUC. In rabbits, three spontaneous abortions and a single total litter loss were observed at the highest maternally toxic dose, which was 7 times the MRHD based on AUC. A single total litter loss occurred at a lower non-maternally toxic dose of 150 mg/kg/day, which was 4 times the MRHD.

No fetal malformations were present at any dose level tested in either species even in the presence of maternal toxicity. At the highest doses tested, the exposure margins were 25 and 7 times the MRHD for the rat and rabbit, respectively. However, because elagolix binds poorly to the rat gonadotropin-releasing hormone (GnRH) receptor (~1000 fold less than to the human GnRH receptor), the rat study is unlikely to identify pharmacologically mediated effects of elagolix on embryofetal development. The rat study is still expected to provide information on potential non-target-related effects of elagolix.

In a pre- and postnatal development study in rats, elagolix was given in the diet to achieve doses of 0, 100, and 300 mg/kg/day (25 per dose group) from gestation day 6 to lactation day 20. There was no evidence of maternal toxicity. At the highest dose, two dams had total litter loss, and one failed to deliver. Pup survival was decreased from birth to postnatal day 4. Pups had lower birth weights, and lower body weight gains were observed throughout the pre-weaning period at 300 mg/kg/day. Smaller body size and effect on startle response were associated with lower pup weights at 300 mg/kg/day. Post-weaning growth, development, and behavioral endpoints were unaffected.

Maternal plasma concentrations in rats on lactation day 21 at 100 and 300 mg/kg/day (47 and 125 ng/mL) were 0.04-fold and 0.1-fold the maximal elagolix concentration (Cmax) in humans at the MRHD. Because the exposures achieved in rats were much lower than the human MRHD, this study is not predictive of potentially higher lactational exposure in humans.

8.2 Lactation

Risk Summary

There is no information on the presence of elagolix or its metabolites in human milk, the effects on the breastfed child, or the effects on milk production. When estrogen and progestins are administered to lactating women, these compounds and/or their metabolites are detected in human milk and can reduce milk production in breast-feeding females. This reduction can occur at any time but is less likely to occur once breast-feeding is well established. Advise the nursing female to use non-hormonal contraception until she discontinues breast-feeding. The developmental and health benefits of breast-feeding should be considered along with the mother’s clinical need for ORIAHNN and any potential adverse effects on the breast-fed child from ORIAHNN or from the underlying maternal condition [see Data].

Data

There is no information on the presence of elagolix or its metabolites in human milk, the effects on the breastfed child, or the effects on milk production. Estrogen administration to nursing women has been shown to decrease the quantity and quality of the breast milk. Detectable amounts of estrogen and progestin have been identified in the breast milk of women receiving estrogen and progestin combinations.

There are no adequate animal data on excretion of elagolix in milk.

8.3 Females and Males of Reproductive Potential

Based on the mechanism of action of elagolix, there is a risk of early pregnancy loss if ORIAHNN is administered to a pregnant woman [see Use in Specific Populations (8.1), Clinical Pharmacology (12.1)].

Pregnancy Testing

ORIAHNN may delay the ability to recognize the occurrence of a pregnancy because it may reduce the intensity, duration, and amount of menstrual bleeding [see Adverse Reactions (6.1)]. Exclude pregnancy before initiating treatment with ORIAHNN. Perform pregnancy testing if pregnancy is suspected during treatment with ORIAHNN and discontinue treatment if pregnancy is confirmed [see Contraindications (4) and Warnings and Precautions (5.8)].

Contraception

Advise women to use non-hormonal contraception during treatment with ORIAHNN and for 28 days after discontinuing ORIAHNN [see Warnings and Precautions (5.8)].

8.4 Pediatric Use

Safety and effectiveness of ORIAHNN in pediatric patients have not been established.

8.6 Renal Impairment

No dose adjustment of ORIAHNN is required in women with any degree of renal impairment or end-stage renal disease (including women on dialysis) [see Clinical Pharmacology (12.3)].

8.7 Hepatic Impairment

ORIAHNN is contraindicated in women with any hepatic impairment or disease [see Contraindications (4)]. The use of estradiol (a component of ORIAHNN) in patients with hepatic impairment, compared to patients with normal hepatic function, is expected to increase the blood levels of estradiol and increase the risk of estradiol-associated adverse reactions. Additionally, the use of elagolix (a component of ORIAHNN) in patients with moderate and severe hepatic impairment, compared to patients with normal hepatic function, increased elagolix exposures 3-fold and 7-fold, respectively, and this increases the risk of elagolix-associated adverse reactions [see Clinical Pharmacology (12.3)].

10 OVERDOSAGE

Overdosage of estrogen and progestin combination products may cause nausea, vomiting, breast tenderness, abdominal pain, drowsiness, fatigue, and withdrawal bleeding. In case of ORIAHNN overdose, monitor the patient for any signs or symptoms of adverse reactions and initiate appropriate symptomatic treatment, as needed.

11 DESCRIPTION

ORIAHNN consists of two capsules: one to be taken orally in the morning (AM) and one to be taken orally in the evening (PM). The AM capsule is white and yellow and contains 300 mg elagolix (equivalent to 310.4 mg of elagolix sodium), 1 mg estradiol, and 0.5 mg norethindrone acetate. The PM capsule is white and light blue and contains 300 mg of elagolix (equivalent to 310 mg of elagolix sodium).

Elagolix

Elagolix sodium is the sodium salt of the active moiety elagolix, a nonpeptide small molecule, GnRH receptor antagonist. Elagolix sodium is chemically described as sodium 4-({(1R)-2-[5-(2-fluoro-3-methoxyphenyl)-3-{[2-fluoro-6-(trifluoromethyl)phenyl]methyl}-4-methyl-2,6-dioxo-3,6-dihydropyrimidin-1(2H)-yl]-1-phenylethyl}amino)butanoate. Elagolix sodium has a molecular formula of C32H29F5N3O5Na and a molecular weight of 653.58. Elagolix free acid has a molecular formula of C32H30F5N3O5 and a molecular weight of 631.60.

Elagolix sodium has the following structural formula:

Elagolix sodium is a white to off-white to light yellow powder and is freely soluble in water.

Estradiol

Estradiol (E2), an estrogen, is a white or almost white crystalline powder. Its chemical name is estra-1,3,5(10)-triene-3,17β-diol with the molecular formula of C18H24O2, and molecular weight of 272.38. The structural formula of E2 is as follows:

Norethindrone acetate

Norethindrone acetate (NETA), a progestin, is a white or yellowish white crystalline powder. Its chemical name is 17β-acetoxy-19-nor-17α-pregn-4-en-20-yn-3-one with the molecular formula of C22H28O3 and molecular weight of 340.46.

ORIAHNN morning (AM) capsules contain the following inactive ingredients: anhydrous sodium carbonate, polyethylene glycol 3350, crospovidone, colloidal silicon dioxide, magnesium stearate, polyvinyl alcohol, titanium dioxide, polyethylene glycol, talc, purified water, lactose monohydrate, starch (corn), copovidone, talc, hypromellose, triacetin, and gelatin capsule shell. The capsule shell contains the following ingredients: FD&C Red #40, FD&C Yellow #5 [see Warnings and Precautions (5.12)], FD&C Yellow #6, titanium dioxide, gelatin, and printing ink (shellac, dehydrated alcohol, isopropyl alcohol, butyl alcohol, propylene glycol, strong ammonia solution, black iron oxide, potassium hydroxide, and purified water).

ORIAHNN evening (PM) capsules contain the following inactive ingredients: anhydrous sodium carbonate, polyethylene glycol 3350, crospovidone, colloidal silicon dioxide, magnesium stearate, polyvinyl alcohol, titanium dioxide, polyethylene glycol, talc, purified water, and gelatin capsule shell. The capsule shell contains the following ingredients: FD&C Blue #2, FDA/E172 yellow iron oxide, titanium dioxide, gelatin, and printing ink (shellac, dehydrated alcohol, isopropyl alcohol, butyl alcohol, propylene glycol, strong ammonia solution, black iron oxide, potassium hydroxide, and purified water).

12 CLINICAL PHARMACOLOGY

12.1 Mechanism of Action

ORIAHNN combines elagolix and estradiol/norethindrone acetate (E2/NETA), a combination of estrogen and progestin.

Elagolix is a GnRH receptor antagonist that inhibits endogenous GnRH signaling by binding competitively to GnRH receptors in the pituitary gland. Administration of elagolix results in dose-dependent suppression of luteinizing hormone (LH) and follicle-stimulating hormone (FSH), leading to decreased blood concentrations of the ovarian sex hormones estradiol and progesterone and reduces bleeding associated with uterine fibroids.

E2 acts by binding to nuclear receptors that are expressed in estrogen-responsive tissues. As a component of ORIAHNN, the addition of exogenous estradiol may reduce the increase in bone resorption and resultant bone loss that can occur due to a decrease in circulating estrogen from elagolix alone.

Progestins such as NETA act by binding to nuclear receptors that are expressed in progesterone-responsive tissues. As a component of ORIAHNN, NETA may protect the uterus from the potential adverse endometrial effects of unopposed estrogen.

12.2 Pharmacodynamics

Estradiol and norethindrone acetate (components of ORIAHNN) may have the following effects:

- Increased thyroxin-binding globulin levels leading to [see Warnings and Precautions (5.11)]:
  ○ Increased circulating total thyroid hormone levels as measured by protein-bound iodine (PBI), thyroxine (T4) levels (by column or by radioimmunoassay), or triiodothyronine (T3) levels by radioimmunoassay
  ○ Decreased T3 resin uptake
  ○ Unaltered free T4 and free T3 concentrations in women with normal thyroid function [see Warnings and Precautions (5.11)].
- Elevated corticosteroid-binding globulin (CBG) and sex hormone-binding globulin (SHBG) leading to increased total circulating corticosteroids and sex steroids, respectively [see Warnings and Precautions (5.11)].
- Possible decreased free testosterone concentrations.
- Possible increased other plasma proteins concentrations (angiotensinogen/renin substrate, alpha-1 antitrypsin, ceruloplasmin).
- Increased plasma high-density lipoprotein (HDL) and HDL2 cholesterol subfraction concentration, reduced low-density lipoprotein concentration, increased triglyceride levels [see Warnings and Precautions (5.9)].
- Accelerated prothrombin time, partial thromboplastin time, and platelet aggregation time; increased platelet count; increased factors II, VII antigen, VIII coagulant activity, IX, X, XII, VII-X complex, and beta-thromboglobulin; decreased levels of anti-factor Xa and antithrombin III, decreased antithrombin III activity, increased levels of fibrinogen and fibrinogen activity; increased plasminogen antigen and activity.

Cardiac Electrophysiology

The effect of elagolix (a component of ORIAHNN) on the QTc interval was evaluated in a randomized, placebo- and positive-controlled, open-label, single-dose, crossover thorough QTc study in 48 healthy adult premenopausal women. Elagolix concentrations in women given a single dose of 1200 mg were 9 times higher than the concentration in women given elagolix 300 mg twice daily. There was no clinically relevant prolongation of the QTc interval.

The effect of estradiol and norethindrone acetate (two components of ORIAHNN) on the QTc interval has not been studied.

12.3 Pharmacokinetics

The pharmacokinetic properties of ORIAHNN in healthy subjects are summarized in Table 4.

The pharmacokinetic parameters under fasting conditions are summarized in Table 5.

Table 4. Pharmacokinetic Properties of ORIAHNN in Healthy Subjects
Absorption
 | Elagolix | Estradiola | Norethindrone
Tmax (h) b,c | 1.5 (1.0 – 4.0) | 2.0 (0.0 - 10.0) | 1.0 (0.5 - 2.0)
Effect of Food
High-fat meald (relative to fasting) | AUC: ↓25%, Cmax: ↓36% | AUC: no change, Cmax: ↓23% | AUC: ↑23%, Cmax: ↓50%
Distribution
% Bound to human plasma proteins | 80 | 98 | 97
Blood-to-plasma ratio | 0.6 | NA | NA
Metabolism
Metabolism | CYP3A (major) Minor pathways include: CYP2D6, CYP2C8, and uridine glucuronosyl transferases (UGTs) | CYP3A (partial) Other pathways include: sulfation and glucuronidation | CYP3A (partial)
Elimination
Major route of elimination | Hepatic metabolism | Hepatic metabolism | Hepatic metabolism
Terminal phase elimination half-life (t 1/2) (h) c, e | 5.9 ± 2.1 | 14.5 ± 6.6 | 9.2 ± 4.0
% of dose excreted in urine | <3 | NA | NA
% of dose excreted in feces | 90 | NA | NA
NA=not available
aBaseline adjusted unconjugated estradiol
bMedian and range
cFollowing administration of a single dose under fasting conditions
dHigh-fat meal is approximately 826 kcal, 52% fat.
eMean ± SD

Table 5. Mean (%CV) Pharmacokinetic Parameters of ORIAHNN
Pharmacokinetic Parameter (Units) | Elagolix 300 mg Twice Dailya N = 8 | Estradiolb 1 mg N = 163 | Norethindroneb 0.5 mg N = 163
Cmax (ng/mL) | 1200 (45) | 0.06 (52) | 6.1 (35)
AUCτ (ng●hr/mL) | 2826 (44) | 0.86 (38) | 23.8 (48)
aData obtained at steady state (Day 21); AUCτ represents the area under the plasma concentration-time curve from 0 to 12 hours post dose.
bData obtained following single dose administration; AUCτ represents AUC from 0 to 24 hours post dose; estradiol: baseline adjusted unconjugated estradiol.
CV: Coefficient of variation
Cmax: Plasma peak concentration

Specific Populations

Patients with Renal Impairment

Elagolix exposures (Cmax and AUC) were not altered by renal impairment. The elagolix mean plasma exposures were similar for women with moderate to severe or end-stage renal disease (including women on dialysis) compared to women with normal renal function.

The effect of renal impairment on the pharmacokinetics of E2/NETA has not been studied.

Patients with Hepatic Impairment

Elagolix exposures (Cmax and AUC) were similar between women with normal hepatic function and women with mild hepatic impairment. Elagolix exposures in women with moderate and severe hepatic impairment were approximately 3-fold and 7-fold, respectively, higher than exposures from women with normal hepatic function.

The use of estradiol in patients with hepatic impairment, compared to patients with normal hepatic function, is expected to increase the estradiol blood levels [see Warnings and Precautions (5.5) and Use in Specific Populations (8.7)].

Racial or Ethnic Groups

No clinically meaningful difference in the pharmacokinetics of elagolix between White and Black subjects or between Hispanics and others was observed. There is no clinically meaningful difference in the pharmacokinetics of elagolix between Japanese and Han Chinese subjects. The effect of race/ethnicity on the pharmacokinetics of E2/NETA has not been studied.

Body Weight/Body Mass Index

Body weight or body mass index does not affect the pharmacokinetics of elagolix.

The effect of body weight/body mass index on the pharmacokinetics of E2/NETA has not been studied.

Drug Interaction Studies

Drug interaction studies were performed with elagolix and other drugs likely to be co-administered and with drugs commonly used as probes for pharmacokinetic interactions. Tables 6 and 7 summarize the pharmacokinetic effects when elagolix was co-administered with these drugs.

Table 6. Drug Interactions: Change in Pharmacokinetics of Elagolix in the Presence of Co-administered Drugs
Co-administered Drug | Co-administered Drug Regimen | Elagolix Regimen | N | Ratio (90% CI)*
Ketoconazole | 400 mg once daily | 150 mg single dose& | 11 | Cmax | AUC
 |  |  |  | 1.77 (1.48 - 2.12) | 2.20 (1.98 - 2.44)
Rifampin** | 600 mg single dose | 150 mg single dose& | 12 | 4.37 (3.62 - 5.28) | 5.58 (4.88 - 6.37)
 | 600 mg once daily |  |  | 2.00 (1.66 - 2.41) | 1.65 (1.45 - 1.89)
CI: Confidence interval
& The elagolix dose in these studies was 0.5 times the approved dose in ORIAHNN (0.25 times the total approved daily dosage of elagolix in ORIAHNN)
* ratios for Cmax and AUC compare co-administration of the medication with elagolix vs. administration of elagolix alone.
**A single dose of 600 mg rifampin inhibits OATP1B1; 600 mg once daily dose of rifampin inhibits OATP1B1 and induces CYP3A.

No clinically significant changes in elagolix exposures were observed when elagolix 300 mg twice daily was co-administered with rosuvastatin (20 mg once daily), sertraline (25 mg once daily), or fluconazole (200 mg single dose). The effect of co-administered rosuvastatin, sertraline, or fluconazole on E2/NETA has not been studied.

Table 7. Drug Interactions: Change in Pharmacokinetics of Co-administered Drug in the Presence of Elagolix
Co-administered Drug | Co-administered Drug Regimen | Elagolix Regimen | N | Ratio (90% CI)*
Digoxin | 0.5 mg single dose | 200 mg twice daily x 10 days | 11 | Cmax | AUC
 |  |  |  | 1.71 (1.53 - 1.91) | 1.26 (1.17 - 1.35)
Rosuvastatin | 20 mg once daily | 300 mg twice daily x 7 days | 10 | 0.99 (0.73 - 1.35) | 0.60 (0.50 - 0.71)
Midazolam | 2 mg single dose | 300 mg twice daily x 11 days | 20 | 0.56 (0.51 - 0.62) | 0.46 (0.41 - 0.50)
 | 2 mg single dose | 150 mg once daily x 13 days | 11 | 0.81 (0.74 - 0.89) | 0.65 (0.58 - 0.72)
Omeprazole | 40 mg single dose | 300 mg twice daily x 9 days | 20 | 1.95 (1.50 - 2.53) | 1.78 (1.39 - 2.27)
CI: Confidence interval
*ratios for Cmax and AUC compare co-administration of the medication with elagolix vs.
administration of the medication alone.

No clinically significant changes in sertraline, fluconazole, bupropion, or transdermal patch E2/NETA 0.51/4.8 mg exposures were observed when co-administered with elagolix 300 mg twice daily.

12.5 Pharmacogenomics

Hepatic uptake of elagolix (a component of ORIAHNN) involves the OATP1B1 transporter protein. Higher plasma concentrations of elagolix have been observed in patients who have two reduced function alleles of the gene that encodes OATP1B1 (SLCO1B1 521T>C) (these patients are likely to have reduced hepatic uptake of elagolix and thus, higher plasma elagolix concentrations). The frequency of the SLCO1B1 521C/C genotype is generally less than 5% in most racial/ethnic groups. Women with this genotype are expected to have approximately 2-fold higher elagolix mean concentrations compared to women with normal transporter function (i.e., SLCO1B1 521T/T genotype). Adverse effects of elagolix have not been fully evaluated in subjects who have two reduced function alleles of the gene that encodes OATP1B1 (SLCO1B1 521T>C).

13 NONCLINICAL TOXICOLOGY

13.1 Carcinogenesis, Mutagenesis, Impairment of Fertility

Elagolix

Two-year carcinogenicity studies conducted in mice (50, 150, or 500 mg/kg/day) and rats (150, 300, or 800 mg/kg/day) that administered elagolix by the dietary route revealed no increase in tumors in mice at up to 11.9-fold the MRHD based on AUC. In the rat, there was an increase in thyroid (male and female) and liver (males only) tumors at the high dose (7.7- to 8.1-fold the MRHD). The rat tumors were likely species-specific and of negligible relevance to humans.

Elagolix was not genotoxic or mutagenic in a battery of tests, including the in vitro bacterial reverse mutation assay, the in vitro mammalian cell forward mutation assay at the thymidine kinase (TK+/-) locus in L5178Y mouse lymphoma cells, and the in vivo mouse micronucleus assay.

In a fertility study conducted in the rat, there was no effect of elagolix on fertility at any dose (50, 150, or 300 mg/kg/day). Based on AUC, the exposure multiple for the MRHD in women compared to the highest dose of 300 mg/kg/day in female rats is approximately 2.9-fold. However, because elagolix has low affinity for the GnRH receptor in the rat [see Use in Specific Populations (8.1)], and because effects on fertility are most likely to be mediated via the GnRH receptor, these data have low relevance to humans.

E2/NETA

Long-term continuous administration of natural and synthetic estrogens in certain animal species increases the frequency of carcinomas of the breast, uterus, cervix, vagina, testis, and liver [see Warnings and Precautions (5.3)].

14 CLINICAL STUDIES

The efficacy of ORIAHNN in the management of heavy menstrual bleeding (HMB) associated with uterine fibroids was demonstrated in two randomized, double-blind, placebo-controlled studies [Study UF-1 (NCT02654054) and Study UF-2 (NCT02691494)] in which 790 premenopausal women with heavy menstrual bleeding received ORIAHNN (elagolix 300 mg, estradiol 1 mg, and norethindrone acetate 0.5 mg in the morning and elagolix 300 mg in the evening) or placebo for 6 months. Heavy menstrual bleeding at baseline was defined as having at least two menstrual cycles with greater than 80 mL of menstrual blood loss (MBL) as assessed by alkaline hematin (AH) method (an objective, validated measure to quantify MBL volume on sanitary products).

In Studies UF-1 and UF-2, the median age of enrolled women was 43 years (ranging from 25 to 53 years); 68% of the women were Black or African American, 29% were White, and 3% were other races.

Menstrual Blood Loss

The primary endpoint in both studies was the proportion of responders, defined as women who achieved both 1) MBL volume less than 80 mL at the Final Month and 2) 50% or greater reduction in MBL volume from Baseline to the Final Month. Final Month was defined as the last 28 days before and including the last treatment visit date or the last dose date. A higher proportion of ORIAHNN-treated women were responders compared to placebo-treated women (Table 8).

Table 8. Proportion of Responders for Reduction in MBL Volume at Final Month in Women with Uterine Fibroids (Studies UF-1 and UF-2)
 | Study UF-1 |  | Study UF-2
 | ORIAHNN N=206 | Placebo N=102 | ORIAHNN N=189 | Placebo N=94
Women with MBL volume < 80 mL and ≥ 50% reduction in MBL volume from Baseline to the Final Month | 68.5% | 8.7% | 76.5% | 10.5%
Difference from placebo % 95% CI P-value | 59.8% (51.1, 68.5) < 0.001 |  | 66.0% (57.1, 75.0) < 0.001
CI: confidence interval

Changes in MBL Volume

Treatment with ORIAHNN resulted in a reduction in mean MBL volume from Baseline at Months 1, 3, and 6 compared to placebo (see Figures 2 and 3).

Figure 2. Monthly Change from Baseline in MBL Volume in Women with Uterine Fibroids (Study UF-1)

Figure 3. Monthly Change from Baseline in MBL Volume in Women with Uterine Fibroids (Study UF-2)

In Study UF-1, mean baseline MBL was 238 mL for ORIAHNN and 255 mL for placebo. In Study UF-2, mean baseline MBL was 228 mL for ORIAHNN and 254 mL for placebo. Women taking ORIAHNN had a mean reduction of MBL volume from Baseline to Final Month in both Studies UF-1 and UF-2 compared to women taking placebo (Study UF-1: -177 mL for ORIAHNN and 1 mL for placebo; Study UF-2: -169 mL for ORIAHNN and -4 mL for placebo).

Suppression of Bleeding

In Studies UF-1 and UF-2, a greater proportion (57% and 61%, respectively) of women receiving ORIAHNN experienced suppression of bleeding, defined as no bleeding (but spotting allowed), at Final Month, compared to 4% and 5%, respectively, of women receiving placebo.

Hemoglobin (Hgb)

In Studies UF-1 and UF-2, a greater proportion of ORIAHNN-treated women who were anemic with baseline Hgb ≤ 10.5 g/dL achieved an increase > 2 g/dL in Hgb from Baseline to Month 6 compared to placebo-treated women (see Table 9). Over 90% of women with baseline Hgb ≤ 10.5 g/dL took supplemental iron.

Table 9. Proportion of Women with Uterine Fibroids with Baseline Hgb ≤ 10.5 g/dL and Increase > 2 g/dL in Hgb at Month 6
 | UF-1 |  | UF-2
 | ORIAHNN n=52 (N=206) | Placebo n=31 (N=102) | ORIAHNN n=48 (N=189) | Placebo n=24 (N=94)
(%) at Month 6 | 62% | 16% | 50% | 21%
Difference from placebo % 95% CI p-value | 45% (27, 64) < 0.001 |  | 29% (8, 51) 0.02
CI: confidence interval
n: number of subjects with Hgb ≤10.5 g/dL at Baseline and had Hgb measurements at Month 6
N: number of subjects in each treatment arm

16 HOW SUPPLIED/STORAGE AND HANDLING

ORIAHNN consists of two capsules: one to be taken in the morning (AM) and one to be taken in the evening (PM).

- morning (AM) capsules are white and yellow, printed with “EL300 AM” and contain elagolix 300 mg, estradiol 1 mg, and norethindrone acetate 0.5 mg.
- evening (PM) capsules are white and light blue, printed with “EL300 PM” and contain elagolix 300 mg.

ORIAHNN is packaged in weekly blister packs. Each blister pack contains seven AM capsules and seven PM capsules. Four blisters are packaged into a carton (NDC 0074-1017-56).

Store at 20°C to 25°C (68°F to 77°F), excursions permitted to 15˚C to 30˚C (59˚F to 86˚F). [See USP Controlled Room Temperature].

Dispose unused medication via a take-back option if available. Otherwise, follow FDA instructions for disposing medication in the household trash, www.fda.gov/drugdisposal. Do NOT flush down the toilet.

17 PATIENT COUNSELING INFORMATION

Advise the patient to read the FDA-approved patient labeling (Medication Guide).

Thromboembolic Disorders and Vascular Events

Advise patients that use of estrogen and progestin combinations may increase the risk of thromboembolic disorders and vascular events, especially in women at high risk for these events [see Boxed Warning, Contraindications (4), Warnings and Precautions (5.1), and Adverse Reactions (6.1)].

Bone Loss

Advise patients about the risk of bone loss. Advise patients that supplementary calcium and vitamin D may be beneficial if dietary intake of calcium and vitamin D is not adequate. Advise patients that oral iron supplement should not be taken at the same time as calcium and vitamin D [see Warnings and Precautions (5.2) and Adverse Reactions (6.1)].

Suicidal Ideation and Exacerbation of Mood Disorders

Advise patients that suicidal ideation and exacerbation of mood disorders may occur with ORIAHNN use. Instruct patients with new onset or worsening depression, anxiety, or other mood changes to promptly seek medical attention [see Warnings and Precautions (5.3) and Adverse Reactions (6.1)].

Liver Injury

Advise patients to promptly seek medical attention in case of signs or symptoms that may reflect liver injury, such as jaundice [see Warnings and Precautions (5.5) and Adverse Reactions (6.1)].

Change in Menstrual Bleeding Pattern

Advise patients that ORIAHNN may delay the recognition of pregnancy because it may reduce the duration and amount of menstrual bleeding. Advise patients to use effective non-hormonal contraception while taking ORIAHNN, for 28 days after discontinuing ORIAHNN, and to discontinue ORIAHNN if pregnancy is diagnosed [see Warnings and Precautions (5.8) and Use in Specific Populations (8.1, 8.3)].

Alopecia

Advise patients that alopecia, hair loss, and hair thinning in no specific pattern, may occur with ORIAHNN use. Advise patients that hair loss and hair thinning may not resolve completely after stopping ORIAHNN. Advise patients to contact their healthcare provider if they have concerns about changes to their hair [see Warnings and Precautions (5.10) and Adverse Reactions (6.1)].

Drug Interactions

Advise patients to inform their healthcare providers of all concomitant medications, including prescription medicines, over-the-counter drugs, vitamins, and herbal products. Advise patients to avoid grapefruit juice while taking ORIAHNN [see Drug Interactions (7)].

ORIAHNN Missed Dose Instructions

Instruct patients about what to do in the event a dose is missed. See “If you miss a dose of ORIAHNN” section in FDA-approved Medication Guide.

ORIAHNN Disposal Instructions

Instruct patients to dispose of unused medication via a take-back option if available or to otherwise follow FDA instructions for disposing of medication in the household trash, www.fda.gov/drugdisposal, and not to flush down the toilet.

Manufactured by AbbVie Inc. North Chicago, IL 60064

ORIAHNN is a trademark of AbbVie Inc.

© 2025 AbbVie Inc. All rights reserved.

20096646

MEDICATION GUIDE
ORIAHNN® (or-ee-ahn)
(elagolix, estradiol, and norethindrone acetate capsules; elagolix capsules)
co-packaged for oral use

What is the most important information I should know about ORIAHNN?
ORIAHNN may cause serious side effects, including:

- cardiovascular conditions
  ○ ORIAHNN may increase your chances of heart attack, stroke, or blood clots, especially if you are over 35 years of age and smoke, have uncontrolled high blood pressure, high cholesterol, diabetes, or are obese. Stop taking ORIAHNN and call your healthcare provider right away or go to the nearest hospital emergency room right away if you have:
  ■ leg pain or swelling that will not go away
  ■ sudden shortness of breath
  ■ double vision, bulging of the eyes, sudden blindness, partial or complete
  ■ pain or pressure in your chest, arm, or jaw
  ■ sudden, severe headache unlike your usual headaches
  ■ weakness or numbness in an arm or leg, or trouble speaking
- bone loss (decreased bone mineral density)
  ○ While you are taking ORIAHNN, your estrogen levels may be low. Low estrogen levels can lead to bone mineral density loss.
  ○ If you have bone loss on ORIAHNN, your bone density may improve after you stop taking ORIAHNN, but complete recovery may not occur. It is unknown if these bone changes could increase your risk for broken bones as you age. For this reason, you should not take ORIAHNN for more than 24 months.
  ○ Your healthcare provider may order an X-ray test called a DXA scan to check your bone mineral density when you start taking ORIAHNN and periodically after you start.
  ○ Your healthcare provider may advise you to take vitamin D and calcium supplements as part of a healthy lifestyle that promotes bone health. Iron supplements should not be taken at the same time that you take vitamin D and calcium supplements.
- effects on pregnancy
  ○ Do not take ORIAHNN if you are trying to become pregnant or are pregnant. It may increase the risk of early pregnancy loss.
  ○ If you think you may be pregnant, stop taking ORIAHNN right away and call your healthcare provider.
  ○ ORIAHNN can decrease your menstrual bleeding or result in no menstrual bleeding at all, making it hard to know if you are pregnant. Watch for other signs of pregnancy such as breast tenderness, weight gain, and nausea.
  ○ ORIAHNN does not prevent pregnancy. You will need to use effective methods of birth control while taking ORIAHNN and for 28 days after you stop taking ORIAHNN. Examples of effective methods can include condoms or spermicide, which do not contain hormones.
  ○ Talk to your healthcare provider about which birth control to use during treatment with ORIAHNN. Your healthcare provider may change the birth control you were on before you start taking ORIAHNN.

What is ORIAHNN?
ORIAHNN is a prescription medicine used to control heavy menstrual bleeding in premenopausal women (before “change of life” or menopause) with uterine fibroids.
It is not known if ORIAHNN is safe and effective in children under 18 years of age.

Do not take ORIAHNN if you:

- have or have had:
  ○ stroke or a heart attack
  ○ a problem that makes your blood clot more than normal
  ○ blood circulation disorder
  ○ certain heart valve problems or heart rhythm abnormalities that can cause blood clots to form in the heart
  ○ blood clots in your legs (deep vein thrombosis), lungs (pulmonary embolism), or eyes (retinal thrombosis)
  ○ high blood pressure not well controlled by medicine
  ○ diabetes with kidney, eye, nerve, or blood vessel damage
  ○ certain kinds of headaches with numbness, weakness, or changes in vision or have migraine headaches with aura if you are over age 35
  ○ breast cancer or any cancer that is sensitive to female hormones
  ○ osteoporosis
  ○ unexplained vaginal bleeding that has not been diagnosed. Your healthcare provider should check any unexplained vaginal bleeding to find out the cause.
  ○ liver problems including liver disease
  ○ smoke and are over 35 years old
- are taking medicines known as OATP1B1 inhibitors that are known or expected to significantly increase the blood levels of elagolix (an ingredient in ORIAHNN). Ask your healthcare provider if you are not sure if you are taking this type of medicine.
- have had a serious allergic reaction to elagolix, estradiol, norethindrone acetate, or any of the ingredients in ORIAHNN. Ask your healthcare provider if you are not sure.
- FD&C Yellow No.5 (tartrazine) is an ingredient in ORIAHNN which may cause an allergic type reaction such as bronchial asthma in some patients who are also allergic to aspirin. See the end of this Medication Guide for a complete list of ingredients in ORIAHNN.

Before you take ORIAHNN, tell your healthcare provider about all of your medical conditions, including if you:

- have or have had:
  ○ broken bones or other conditions that may cause bone problems.
  ○ depression, mood swings, or suicidal thoughts or behavior.
  ○ yellowing of the skin or eyes (jaundice) or jaundice caused by pregnancy (cholestasis of pregnancy).
- are scheduled for surgery. ORIAHNN may increase your risk of blood clots after surgery. Your healthcare provider may advise you to stop taking ORIAHNN before you have surgery. If this happens, talk to your healthcare provider about when to restart ORIAHNN after surgery.
- are pregnant or think you may be pregnant.
- are breastfeeding. It is not known if ORIAHNN can pass into your breastmilk. Talk to your healthcare provider about the best way to feed your baby if you take ORIAHNN.

Tell your healthcare provider about all the medicines you take, including prescription and over-the-counter medicines, vitamins, and herbal supplements.
Women on thyroid or cortisol replacement therapy may need increased doses of the hormone.
Know the medicines you take. Keep a list of your medicines with you to show to your healthcare provider and pharmacist when you get a new medicine.

How should I take ORIAHNN?

- Take ORIAHNN exactly as your healthcare provider tells you to take it.
- Your healthcare provider will give you a pregnancy test before you start taking ORIAHNN or will have you start taking ORIAHNN within 7 days after you start your period.
- Take 1 white and yellow ORIAHNN capsule in the morning and 1 white and light blue ORIAHNN capsule in the evening each day.
- Take ORIAHNN at about the same time each morning and evening with or without food.
- If you take too much ORIAHNN, call your healthcare provider or go to the nearest hospital emergency room right away.

If you miss a dose of ORIAHNN (morning or evening capsules):

- Take the missed dose within 4 hours of the time that it was supposed to be taken. Then take the next dose at the usual time.
- If more than 4 hours have passed since you usually take the morning or evening dose, skip the missed dose. Take your next dose at the usual time.
- Do not take 2 doses to make up for the missed dose.

What should I avoid while taking ORIAHNN?

- Avoid grapefruit and grapefruit juice during treatment with ORIAHNN since they may affect the level of ORIAHNN in your blood, which may increase side effects.

What are the possible side effects of ORIAHNN?
ORIAHNN may cause serious side effects including:

- See “What is the most important information I should know about ORIAHNN?”
- suicidal thoughts, suicidal behavior, and worsening of mood. ORIAHNN may cause suicidal thoughts or actions. Call your healthcare provider or get emergency medical help right away if you have any of these symptoms, especially if they are new, worse, or bother you:
  ○ thoughts about suicide or dying
  ○ attempts to commit suicide
  ○ new or worse depression
  ○ new or worse anxiety
  ○ other unusual changes in behavior or mood

Pay attention to any changes, especially sudden changes in your mood, behaviors, thoughts, or feelings.

- abnormal liver tests. Call your healthcare provider right away if you have any of these signs and symptoms of liver problems:
  ○ jaundice
  ○ dark amber-colored urine
  ○ feeling tired (fatigue or exhaustion)
  ○ nausea and vomiting
  ○ generalized swelling
  ○ right upper stomach area (abdomen) pain
  ○ bruising easily
- high blood pressure. You should see your healthcare provider to check your blood pressure regularly.
- gallbladder problems (cholestasis), especially if you had cholestasis of pregnancy.
- increases in blood sugar, cholesterol and fat (triglyceride) levels.
- hair loss (alopecia). Hair loss and hair thinning can happen while taking ORIAHNN and it can continue even after you stop taking ORIAHNN. It is not known if this hair loss or hair thinning is reversible. Talk to your healthcare provider if this is a concern for you.
- changes in laboratory tests including thyroid and other hormone, cholesterol, and blood clotting tests.

The most common side effects of ORIAHNN include: hot flushes, headache, fatigue, and irregular periods.
These are not all the possible side effects of ORIAHNN. For more information, ask your healthcare provider or pharmacist.
Call your healthcare provider for medical advice about side effects. You may report side effects to FDA at 1-800-FDA-1088.

How should I store ORIAHNN?

- Store ORIAHNN at room temperature between 68°F to 77°F (20°C to 25°C).
- Do not keep medicine that is out of date or that you no longer need.
- Dispose of unused medicines through community take-back disposal programs when available. If no community take-back disposal program is available go to www.fda.gov/drugdisposal for information on how to dispose of ORIAHNN the right way.
- Do not flush ORIAHNN down the toilet.

Keep ORIAHNN and all medicines out of the reach of children.

General information about the safe and effective use of ORIAHNN.
Medicines are sometimes prescribed for purposes other than those listed in a Medication Guide. Do not use ORIAHNN for a condition for which it was not prescribed. Do not give ORIAHNN to other people, even if they have the same symptoms that you have. It may harm them. You can ask your pharmacist or healthcare provider for information about ORIAHNN that is written for health professionals.

What are the ingredients in ORIAHNN?
Yellow/White AM Capsule:
Active ingredient: elagolix, estradiol, norethindrone acetate.
Inactive ingredients: anhydrous sodium carbonate, polyethylene glycol 3350, crospovidone, colloidal silicon dioxide, magnesium stearate, polyvinyl alcohol, titanium dioxide, polyethylene glycol, talc, purified water, lactose monohydrate, starch (corn), copovidone, talc, hypromellose, triacetin, and a gelatin capsule shell. The capsule shell contains the following ingredients: FD&C Red #40, FD&C Yellow #5, FD&C Yellow #6, titanium dioxide, gelatin, and printing ink (shellac, dehydrated alcohol, isopropyl alcohol, butyl alcohol, propylene glycol, strong ammonia solution, black iron oxide, potassium hydroxide, and purified water).
Light Blue/White PM Capsule:
Active ingredient: elagolix.
Inactive ingredients: anhydrous sodium carbonate, polyethylene glycol 3350, crospovidone, colloidal silicon dioxide, magnesium stearate, polyvinyl alcohol, titanium dioxide, polyethylene glycol, and talc, purified water, and a gelatin capsule shell. The capsule shell contains the following ingredients: FD&C Blue #2, FDA/E172 yellow iron oxide, titanium dioxide, gelatin, and printing ink (shellac, dehydrated alcohol, isopropyl alcohol, butyl alcohol, propylene glycol, strong ammonia solution, black iron oxide, potassium hydroxide, and purified water).

Manufactured by AbbVie Inc. North Chicago, IL 60064
ORIAHNN is a trademark of AbbVie Inc.
For more information, go to www.ORIAHNN.com or call 1-844-674-2466.

This Medication Guide has been approved by the U.S. Food and Drug Administration.

12/2025

20096646

PACKAGE LABEL

NDC 0074-1017-56

Rx only

56 CAPSULES

FOR 28 DAYS IN 4 WEEKLY BLISTER PACKS

Oriahnn®

elagolix, estadiol and norethindrone acetate capsules and elagolix capsules 300 mg/1 mg/0.5 mg and 300 mg

Co-Packaged for Oral Use

300 mg / 1 mg / 0.5 mg 300mg

*Elagolix 300 mg (equivalent to 310 mg of elagolix sodium)

Contains FD&C Yellow No. 5 (Tartrazine) as a color additive

Each weekly blister pack contains 7 capsules to be taken in the morning

Each capsule contains elagolix* (300 mg), estradiol (1 mg) and norethindrone acetate (0.5 mg)

Each weekly blister pack contains 7 capsules to be taken in the evening

Each capsule contains elagolix* (300 mg)

PACKAGE LABEL

NDC 0074-1017-14

Rx only

14 CAPSULES

FOR 7 DAYS

Oriahnn®

elagolix, estadiol and norethindrone acetate capsules and elagolix capsules 300 mg/1 mg/0.5 mg and 300 mg

Co-Packaged for Oral Use

Each pack contains 7 capsules of elagolix* (300 mg),
estradiol (1mg), and norethindrone acetate (0.5 mg),
and 7 capsules of elagolix* 300 mg in a weekly blister pack for 1 week of treatment

Contains FD&C Yellow No. 5 (Tartrazine) as a color additive

PROFESSIONAL SAMPLE. NOT FOR SALE.